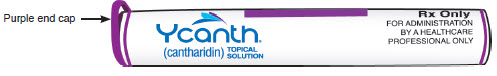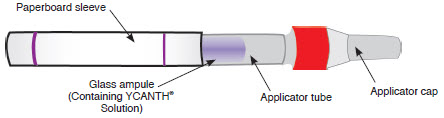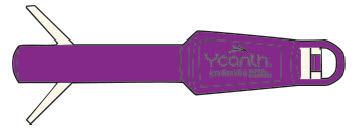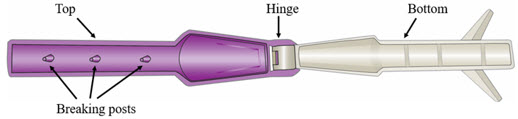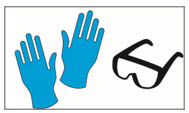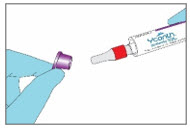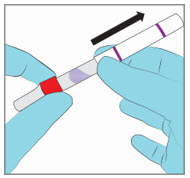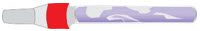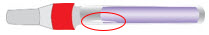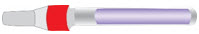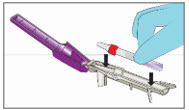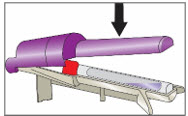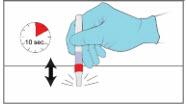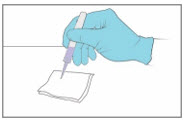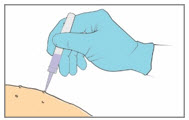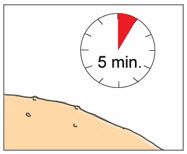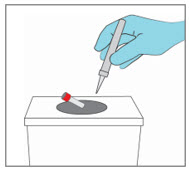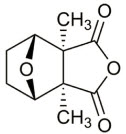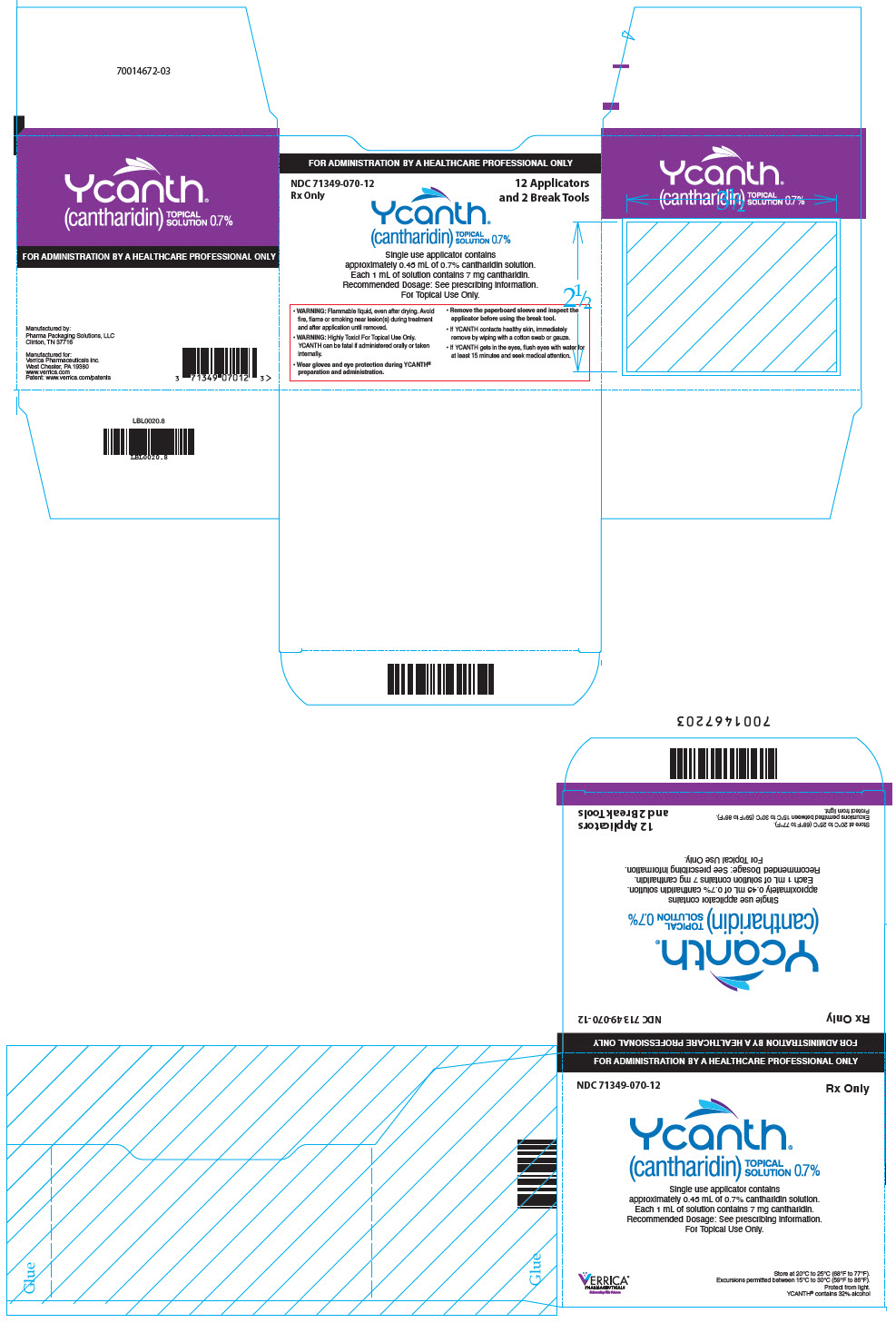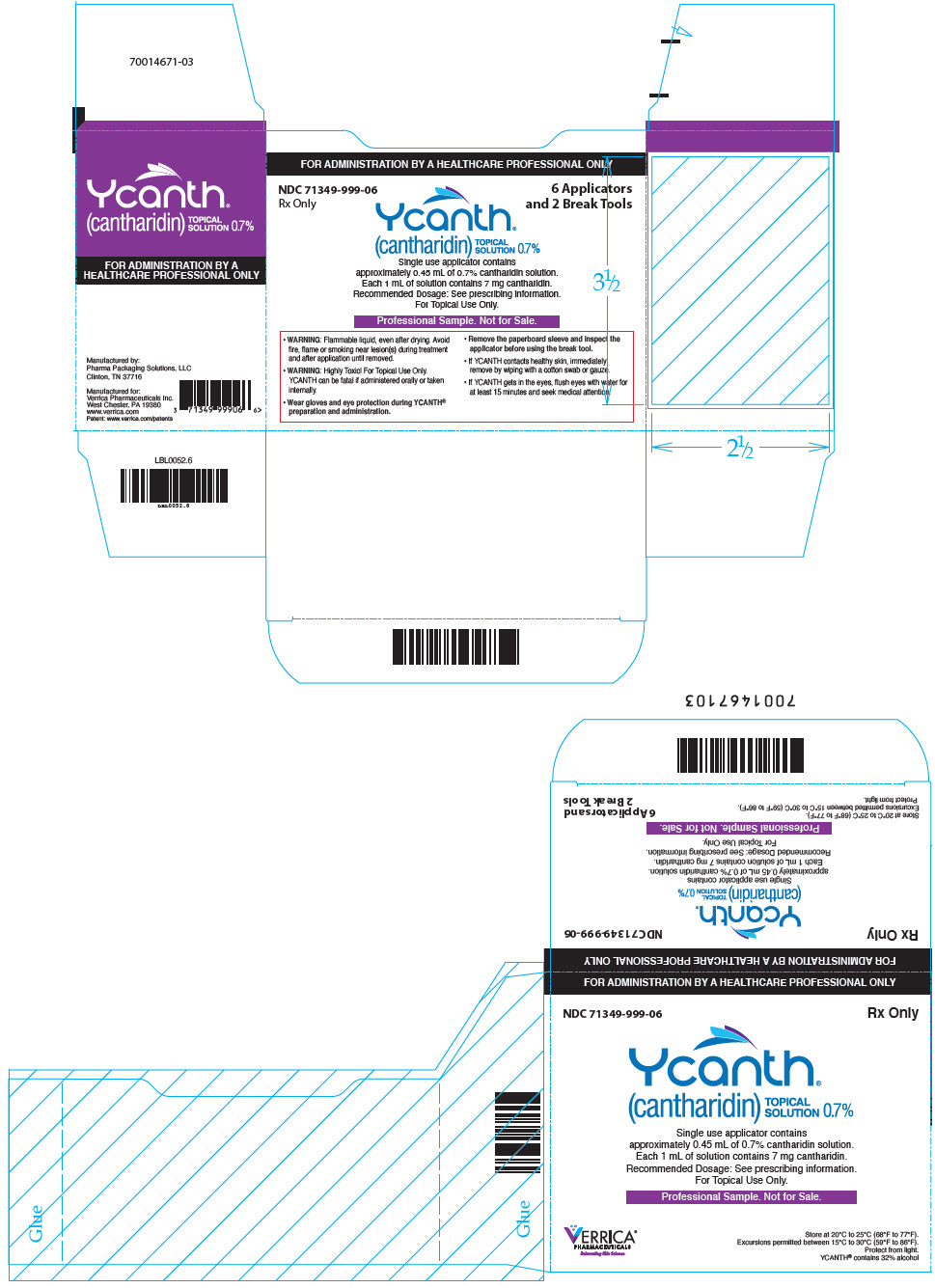 DRUG LABEL: YCANTH
NDC: 71349-070 | Form: SOLUTION
Manufacturer: Verrica Pharmaceuticals Inc.
Category: prescription | Type: HUMAN PRESCRIPTION DRUG LABEL
Date: 20241113

ACTIVE INGREDIENTS: Cantharidin 3.20 mg/0.45 mL

HIGHLIGHTS OF PRESCRIBING INFORMATION

These highlights do not include all the information needed to use YCANTH safely and effectively. See full prescribing information for YCANTH.
YCANTH® (cantharidin) topical solution
Initial U.S. Approval: 2023

1 INDICATIONS AND USAGE

YCANTH is indicated for the topical treatment of molluscum contagiosum in adult and pediatric patients 2 years of age and older. (1)

2 DOSAGE AND ADMINISTRATION

- All healthcare professionals should receive instruction and training prior to preparation and administration of YCANTH. (2.1)
- For topical use only. Not for oral, mucosal, or ophthalmic use. (2.1)
- Apply a single application directly to each lesion every 3 weeks as needed. (2.2)
- Do not use more than two applicators during a single treatment session. (2.2)
- Remove with soap and water 24 hours after treatment. (2.2)
- For additional instructions on preparation and administration of YCANTH, see Full Prescribing Information. (2.1, 2.2, 2.3)

3 DOSAGE FORMS AND STRENGTHS

Topical solution: 0.7% cantharidin. (3)

4 CONTRAINDICATIONS

None

5 WARNINGS AND PRECAUTIONS

- Toxicities Associated with Inappropriate Administration: Life threatening or fatal toxicities can occur if administered orally. Avoid contact with the treatment area, including oral contact, after treatment. Ocular toxicity can occur if YCANTH comes in contact with eyes. If YCANTH gets in eyes, flush eyes with water for at least 15 minutes. (5.1)
- Local Skin Reactions: Reactions at the application site have included vesiculation, pruritus, pain, discoloration, and erythema. Avoid application near eyes and mucosal tissue, and to healthy skin. If YCANTH contacts any unintended surface, or healthy skin, immediately remove. If severe local skin reactions occur, remove prior to 24 hours after treatment. (5.2)
- Flammability: YCANTH is flammable, even after drying. Avoid fire, flame or smoking near lesion(s) during treatment and after application until removed. (5.3)

6 ADVERSE REACTIONS

Most common (incidence ≥1%) adverse reactions are the following local skin reactions at the application site: vesiculation, pain, pruritus, scabbing, erythema, discoloration, application site dryness, edema, and erosion. (6.1)

To report SUSPECTED ADVERSE REACTIONS, contact Verrica Pharmaceuticals Inc. at 1-877-837-7422 or FDA at 1-800-FDA-1088 or www.fda.gov/medwatch. Local skin reactions are expected and should be reported if they are severe.

FULL PRESCRIBING INFORMATION

1 INDICATIONS AND USAGE

YCANTH is indicated for the topical treatment of molluscum contagiosum in adult and pediatric patients 2 years of age and older.

2 DOSAGE AND ADMINISTRATION

2.1 Important Administration Instructions

- All healthcare professionals should receive instruction and training prior to preparation and administration of YCANTH.
- YCANTH is for topical use only.
- YCANTH is not for oral, mucosal, or ophthalmic use. Avoid contact with the treatment area, including oral contact, after YCANTH treatment. Do not apply YCANTH near the eyes [see Warnings and Precautions (5.1), Overdosage (10)].
- If YCANTH contacts any unintended surface, including healthy skin, immediately remove by wiping with a cotton swab or gauze. Avoid other topical products on treated areas until 24 hours after YCANTH treatment or until washing [see Warnings and Precautions (5.2)].
- Avoid fire, flame or smoking near lesion(s) during treatment [see Warnings and Precautions (5.3)].

2.2 Dosage and Administration Overview

- Regarding YCANTH dosage and administration:
  - Use nitrile or vinyl gloves and eye protection during preparation and administration.
  - Apply topically as a single application to cover each lesion. Use no more than two YCANTH applicators during a single treatment session.
  - Remove with soap and water 24 hours after treatment. Administer YCANTH every 3 weeks as needed.
  - Do not cover any treated lesions with bandages.
  - If severe blistering, severe pain, or other severe adverse reactions occur, remove YCANTH with soap and water prior to 24 hours after treatment [see Warnings and Precautions (5.2)].
- Regarding use of the YCANTH applicator and break tool:
  - Do not reuse the applicator. The applicator is for a single treatment session only.
  - Do not attempt to use a clogged applicator.
  - Do not cut or modify the applicator in any way; doing so could reduce dispensing control.
  - Do not remove the applicator cap prior to breaking the glass ampule.
  - If any damage or leaks are observed on the applicator, applicators should be discarded in a sharps container and handled in accordance with accepted medical practice and applicable law. The YCANTH Break Tool should be managed as solid waste and placed in plastic recycling containers or the general trash.

2.3 Dosage and Administration Instructions

Instructions for preparing the YCANTH Applicator and administering the YCANTH Solution are presented below.

YCANTH includes the following components [see How Supplied/Storage and Handling (16.1)]:

Outer Protective Tube

The YCANTH Applicator

The YCANTH Break Tool

Step 1. Put on Personal Protective Equipment (PPE)

- Put on gloves and eye protection.

Step 2. Remove the YCANTH Applicator from Outer Protective Tube

- Use pull ring to remove purple end cap out of white outer protective tube.
- DO NOT remove the applicator cap.
- Slide the YCANTH Applicator out of the outer protective tube.

Step 3. Remove the Paperboard Sleeve

- Completely remove the white paperboard sleeve so that the glass ampule is visible.
- DO NOT remove the applicator cap prior to breaking the glass ampule.

Step 4. Inspect for Damage

- Inspect the YCANTH Applicator for the following types of damage:

Broken glass ampule

Cut or cracked applicator tube

No damage (for reference)

- If any damage is observed, dispose of the YCANTH applicators in a sharps container and handle in accordance with accepted medical practice and applicable law.

Step 5. Break Ampule using the YCANTH Break Tool

- Set the YCANTH Break Tool on a horizontal surface.
- Ensure the applicator cap is in place.
- Place the YCANTH Applicator in the YCANTH Break Tool with the cap pointing toward the hinge.
- Press down firmly on the YCANTH Break Tool until a snap is heard.
- Open the YCANTH Break Tool and remove the YCANTH Applicator.
- If any leaks are observed, applicators should be discarded in a sharps container and handled in accordance with accepted medical practice and applicable law.

Step 6. Tap YCANTH Applicator to move YCANTH Solution

- Gently tap the capped end of the YCANTH Applicator on a horizontal surface for approximately 10 seconds or until the YCANTH Solution has collected at the bottom of the applicator tube.

Step 7. Test the YCANTH Applicator

- Remove the applicator cap.
- Gently squeeze the applicator tube to apply a droplet to a paper towel or gauze to confirm the YCANTH Applicator is working properly.

Step 8. Apply the YCANTH Solution

- Apply a small droplet of the YCANTH Solution onto a molluscum lesion.
- Use the applicator tip to spread the solution to cover the entire lesion.
- Repeat the application until all lesions have been treated.
  - If YCANTH Solution contacts any unintended surface, including healthy skin, immediately remove by wiping with a cotton swab or gauze.
  - DO NOT attempt to use a clogged YCANTH Applicator.

Step 9. Allow YCANTH Solution to Dry

- Allow the YCANTH Solution to completely dry (up to 5 minutes) before contacting healthy skin to avoid transference.
- DO NOT cover any treated lesions with bandages.

Step 10. Dispose of the YCANTH Applicator

- Applicators should be discarded in a sharps container and handled in accordance with accepted medical practice and applicable law.
- DO NOT reuse the YCANTH Applicator.

YCANTH Break Tool Maintenance

- Wipe the surfaces of the YCANTH Break Tool with 70% isopropyl alcohol following each use.
- Inspect the YCANTH Break Tool for damage (e.g., cracks in plastic, missing or broken breaking posts) and function (e.g., hinge) prior to each use.
- After 12 uses or if any damage is observed, the YCANTH Break Tool should be managed as solid waste and placed in plastic recycling containers or the general trash.
- If needed, contact Verrica Pharmaceuticals Inc. at 1-973-298-1390 to request additional YCANTH Break Tools.

3 DOSAGE FORMS AND STRENGTHS

Topical solution 0.7%: Each mL of YCANTH contains 7 mg (0.7%) of cantharidin in a light violet to dark purple, slightly viscous liquid.

4 CONTRAINDICATIONS

None

5 WARNINGS AND PRECAUTIONS

5.1 Toxicities Associated with Inappropriate Administration

YCANTH is for topical use only. YCANTH is not for oral, mucosal, or ophthalmic use.

Life threatening or fatal toxicities can occur if YCANTH is administered orally [see Overdosage (10)]. Adverse reactions to oral ingestion of cantharidin have included renal failure, blistering and severe damage to the gastrointestinal tract, coagulopathy, seizures, and flaccid paralysis. Advise patients and/or caregivers to avoid oral contact and to avoid touching lesions after YCANTH treatment and to seek medical attention immediately if YCANTH is accidently ingested.

Ocular toxicity can occur if YCANTH comes in contact with the eyes. Adverse reactions from contact of YCANTH with the eyes can include corneal necrosis, ocular perforation, and deep ocular injuries. Do not apply YCANTH near or to the eyes. If YCANTH comes in contact with the eyes, flush eyes with water for at least 15 minutes and seek medical attention immediately.

5.2 Local Skin Reactions

YCANTH is a vesicant. Local skin reactions at the application site were observed in 97% of subjects treated with YCANTH during clinical trials. Local skin reactions included vesiculation, pruritus, pain, discoloration, and erythema [see Adverse Reactions (6.1)].

Avoid application near the eyes and mucosal tissues, and to adjacent healthy skin. If YCANTH contacts any unintended surface, including healthy skin, immediately remove by wiping with a cotton swab or gauze.

Avoid other topical products (e.g. creams, lotions, or sunscreen) on treated areas until 24 hours after YCANTH treatment or until washing. Application of other topical products could spread YCANTH and cause blistering or other adverse reactions to healthy skin.

If severe blistering, severe pain or other severe adverse reactions occur, remove YCANTH prior to the recommended 24 hours after administration by washing with soap and water.

5.3 Flammability

YCANTH is a flammable liquid, even after drying. Avoid fire, flame or smoking near lesion(s) during treatment and after application until removed.

6 ADVERSE REACTIONS

The following adverse reactions are described elsewhere in the labeling:

- Local Skin Reactions [see Warnings and Precautions (5.2)]

6.1 Clinical Trials Experience

Because clinical trials are conducted under widely varying conditions, adverse reaction rates observed in the clinical trials of a drug cannot be directly compared to rates in the clinical trials of another drug and may not reflect the rates observed in practice.

YCANTH was studied in two randomized, double-blind, placebo-controlled phase 3 trials, Trial 1 (NCT03377790) and Trial 2 (NCT03377803) (n = 266, and n = 262, respectively) in subjects with molluscum contagiosum. Most patients received a single 24-hour dermal administration of YCANTH or vehicle for each lesion every 3 weeks for up to 4 treatments. YCANTH Solution or vehicle were removed prior to the 24-hour timepoint in 109/311 (35%) subjects treated with YCANTH Solution and 46/216 (21%) subjects treated with vehicle due to treatment-emergent adverse events.

Table 1 presents the percentage of subjects with selected adverse reactions (incidence ≥ 1%) by the most severe grade reported during Trial 1 and Trial 2. Adverse reactions were primarily local skin reactions at the application site. Local skin reactions at the application site were observed in 97% of subjects treated with YCANTH during both trials.

Table 1. Percentage of Subjects with Selected Adverse Reactions (Incidence ≥1%) by Severity in Trial 1 and Trial 2 (Safety Population)
 | YCANTH N=311 |  |  | Vehicle N=216
Preferred Term Name | Mild | Moderate | Severe | Mild | Moderate | Severe
Application site vesicles | 60% | 32% | 4% | 27% | 2% | 0%
Application site pain and pain | 41% | 20% | 2% | 16% | 1% | 0%
Application site pruritus and pruritus | 47% | 8% | 1% | 30% | 7% | 0%
Application site scab and scab | 39% | 9% | 0% | 20% | 1% | 0%
Application site erythema and erythema | 24% | 21% | <1% | 20% | 7% | 0%
Application site discoloration | 28% | 4% | <1% | 12% | 1% | 0%
Application site dryness | 19% | 2% | 0% | 14% | 1% | 0%
Application site edema | 7% | 3% | 0% | 3% | 1% | 0%
Application site erosion | 6% | 1% | 0% | 1% | 0% | 0%
Contact dermatitis | 0% | 1% | 0% | 0% | 0% | 0%

There were no serious adverse reactions reported in the two controlled trials.

The discontinuation rate due to an adverse reaction was 2.3% among subjects treated with YCANTH and 0.5% among subjects treated with vehicle.

8 USE IN SPECIFIC POPULATIONS

8.1 Pregnancy

Risk Summary

There are no available data with use of YCANTH in pregnant women to evaluate for a drug-associated risk of major birth defects, miscarriage or adverse maternal or fetal outcomes. Animal reproduction studies were not conducted with cantharidin. Given that systemic exposure to cantharidin following topical administration is low, maternal use is not expected to result in fetal exposure to the drug [see Clinical Pharmacology (12.3)].

The background risk of major birth defects and miscarriage for the indicated population is unknown. All pregnancies have a background risk of birth defect, loss, or other adverse outcomes. In the U.S. general population, the estimated background risk of major birth defects and miscarriage in clinically recognized pregnancies is 2% to 4% and 15% to 20%, respectively.

8.2 Lactation

Risk Summary

Avoid application of YCANTH topical solution to areas with increased risk for potential ingestion by or ocular exposure to the breastfeeding child. There are no data on the presence of cantharidin in either human or animal milk, or the effects on the breastfed infant or on milk production. Breastfeeding is not expected to result in exposure of the child to the drug due to the low systemic absorption of YCANTH following topical administration [see Clinical Pharmacology (12.3)]. The developmental and health benefits of breastfeeding should be considered along with the mother's clinical need for YCANTH topical solution and any potential adverse effects on the breastfeeding child from YCANTH topical solution or from the underlying maternal condition.

8.4 Pediatric Use

Risk Summary

The safety and effectiveness of YCANTH for the treatment of molluscum contagiosum have been established in pediatric patients aged 2 years and older. The use of YCANTH in pediatric patients is supported by results from adequate and well-controlled trials in patients 2 years of age and older; although the safety and efficacy of drug use for longer than 12 weeks has not been established [see Clinical Studies (14)].

The safety and efficacy in pediatric patients below the age of 2 years have not been established.

8.5 Geriatric Use

Risk Summary

YCANTH has not been studied in geriatric patients.

10 OVERDOSAGE

Oral ingestion of cantharidin has resulted in renal failure, blistering and severe damage to the gastrointestinal tract, coagulopathy, seizures, and flaccid paralysis.

In the event that YCANTH topical solution is ingested, patients should seek medical attention immediately and contact a Poison Control Center (1-800-222-1222) or a medical toxicologist for additional overdosage management recommendations.

11 DESCRIPTION

YCANTH (cantharidin) topical solution is a light violet to dark purple, slightly viscous liquid for topical administration.

Each mL of YCANTH topical solution contains 7 mg of active ingredient cantharidin (0.7%), a lipophilic compound. Cantharidin is a white to off-white solid at room temperature and is only very slightly soluble in water.

The chemical name for cantharidin is 1,2-dimethyl-3,6-epoxyperhydrophthalic anhydride. The molecular weight is 196.20 g/mol and the molecular formula is C10H12O4. The structural formula for cantharidin is represented below:

The inactive ingredients of YCANTH topical solution are acetone, camphor, castor oil, denatonium benzoate, ethanol (32%), gentian violet, hydroxypropyl cellulose, and nitrocellulose. The inactive ingredient denatonium benzoate is an oral deterrent to help mitigate the risk of accidental ingestion.

12 CLINICAL PHARMACOLOGY

12.1 Mechanism of Action

The mechanism of action of cantharidin in the treatment of molluscum contagiosum is unknown.

12.2 Pharmacodynamics

Cantharidin is a vesicant. The pharmacodynamics of cantharidin in the treatment of molluscum contagiosum are unknown.

12.3 Pharmacokinetics

Pharmacokinetics of cantharidin were assessed in 16 subjects aged 2 years and older with at least 21 molluscum contagiosum lesions at baseline. Subjects were administered a single, dermal application of cantharidin solution to each lesion. The average number of lesions treated for subjects in the exposure treatment group was 47.4 (median was 35.0).

Cantharidin was not detectable in 15 out of 16 subjects. Only one subject had a detectable cantharidin plasma level of 3.391 ng/mL at the 2-hour post-dose.

Drug Interaction Studies

No studies evaluating the drug interaction potential of cantharidin have been conducted.

13 NONCLINICAL TOXICOLOGY

13.1 Carcinogenesis, Mutagenesis, Impairment of Fertility

Carcinogenicity studies have not been conducted with cantharidin.

Cantharidin was not mutagenic in a bacteria reverse mutation (Ames) assay. An in vitro chromosomal aberration assay in human lymphocytes with cantharidin was inconclusive. Cantharidin was positive in an in vitro micronucleus assay in TK6 cells, primarily through an aneugenic mechanism.

The effects of cantharidin on fertility have not been evaluated.

14 CLINICAL STUDIES

In two double-blind, randomized, placebo-controlled trials (Trial 1 [NCT03377790] and Trial 2 [NCT03377803]), 528 subjects ages 2 years and older with molluscum contagiosum were randomized by household to treatment with either YCANTH or vehicle. Subjects ranged from 2 to 60 years of age, with a median age of 6. 51% of subjects were male and 91% were Caucasian. The baseline lesion count among subjects ranged from 1 to 184, with a mean of 23 and 19 lesions among subjects in Trial 1 and Trial 2, respectively.

Subjects' lesions were treated with either YCANTH or vehicle at intervals of approximately 21 days until complete clearance of the lesion or for a maximum of 4 applications (on Days 1, 21, 42, and 63). Study drug solution was applied and left on the lesions for approximately 24 hours before the lesions were washed with soap and water.

A healthcare professional who was blinded to the treatment group counted the number of lesions at each visit. The primary efficacy endpoint was the proportion of patients achieving complete clearance of all treated molluscum contagiosum lesions by Day 84. The secondary efficacy endpoints were the proportions of patients achieving complete clearance of all treated molluscum contagiosum lesions at Day 63, Day 42, and Day 21. Table 2 presents the efficacy results for Trial 1 and Trial 2.

Table 2. Percentage of Subjects Exhibiting Complete Clearance of Treatable Molluscum Contagiosum Lesions in Trial 1 and Trial 2 (Intent-to-Treat Population)
 | Trial 1 |  |  | Trial 2
 | YCANTH N = 160 | Vehicle N = 106 | Treatment Difference (95% CI) [Treatment difference and 95% CI based on Generalized Estimating Equations (GEE) model for logistic regression with an exchangeable working correlation structure, a factor for treatment, and repeated measurements allowed for a household. Subjects with missing data are imputed as non-responders.] | YCANTH N = 150 | Vehicle N = 112 | Treatment Difference (95% CI)
Day 84 | 46% | 18% | 29% (19%, 38%) | 54% | 13% | 40% (30%, 51%)
Day 63 | 32% | 17% | 15% (4%, 25%) | 28% | 5% | 23% (15%, 32%)
Day 42 | 21% | 9% | 10% (2%, 19%) | 13% | 4% | 9% (3%, 16%)
Day 21 | 11% | 4% | 8% (2%, 14%) | 5% | 2% | 3% (-1%, 8%)
CI = confidence interval.

16 HOW SUPPLIED/ STORAGE AND HANDLING

16.1 How Supplied

YCANTH topical solution is supplied in a sealed glass ampule contained within a single-use applicator and enclosed in a protective paperboard sleeve. Each ampule of YCANTH contains approximately 0.45 mL of 0.7% cantharidin solution. Each mL of YCANTH contains 7 mg cantharidin (0.7%). A YCANTH Break Tool is co-packaged as 2 units per each 6 count and 12 count carton of applicators and 1 unit per each 1 count carton with 1 applicator.

A listing of the available carton packages is provided in Table 3.

Table 3. Available Carton Configurations for YCANTH
Dosage Strength | Single-Use Applicator | Single Applicator NDC (Each) | Number of YCANTH Applicators (Each) per Carton | YCANTH Break Tool Part Reference Number | Number of YCANTH Break Tools (Each) per Carton | NDC
0.7% (7 mg/mL) | 1 each | 71349-070-01 | 1 | 71349-000-01 | 1 | 71349-070-11
0.7% (7 mg/mL) | 1 each | 71349-070-01 | 6 | 71349-000-01 | 2 | 71349-070-06
0.7% (7 mg/mL) | 1 each | 71349-070-01 | 12 | 71349-000-01 | 2 | 71349-070-12

Individual YCANTH Break Tools are available separately (Part Reference Number 71349-000-01).

To request additional YCANTH Break Tools, contact Verrica Pharmaceuticals at 1-973-298-1390.

16.2 Storage and Handling

Store at 20°C to 25°C (68° to 77°F); excursions permitted between 15°C to 30°C (59°F to 86°F) [see USP Controlled Room Temperature], protect from light.

17 PATIENT COUNSELING INFORMATION

Advise the patient and/or caregivers to read the FDA-approved patient labeling (Patient Information).

Toxicities Associated with Inappropriate Administration

Inform patients and/or caregivers that YCANTH can be fatal if ingested orally. Instruct patients and/or caregivers to avoid oral contact and to avoid touching lesions after YCANTH treatment. If YCANTH is accidentally ingested, inform patients and/or caregivers to seek medical attention immediately.

Advise patients and/or caregivers that severe eye injury can occur if YCANTH gets into the eyes. If YCANTH gets in the eyes, advise patients and/or caregivers to flush eyes with water for at least 15 minutes and seek medical attention immediately [see Warnings and Precautions (5.1)].

Local Skin Reactions

Inform patients and/or caregivers that treatment with YCANTH can lead to local skin reactions [see Adverse Reactions (6.1)].

Advise patients and/or caregivers not to use other topical products (e.g. creams, lotions, or sunscreen) until 24 hours after YCANTH treatment or until washing. Advise patients and/or caregivers to remove YCANTH with soap and water prior to 24 hours after treatment and contact the healthcare provider if severe blistering, severe pain or other severe adverse reactions occur [see Warnings and Precautions (5.2)].

Flammability

Inform patients and/or caregivers that YCANTH is flammable, even after drying. Instruct patients and/or caregivers to avoid fire, flame, or smoking near the lesions treated with YCANTH until YCANTH is removed [see Warnings and Precautions (5.3)].

Important Dosage and Administration Information

Inform patients and/or caregivers to remove YCANTH with soap and water 24 hours after treatment. Inform patients and/or caregivers that more than one YCANTH treatment may be necessary [see Dosage and Administration (2.2)].

Manufactured by:
Pharmaceutical Packaging Solutions
341 JD Yarnell
Industrial Pkwy,
Clinton, TN 37716

For:
Verrica Pharmaceuticals Inc.
44 West Gay Street, Suite 400
West Chester, PA 19380

YCANTH and VERRICA are registered trademarks of Verrica Pharmaceuticals Inc.

Copyright © 2024 Verrica Pharmaceuticals Inc.
All rights reserved.

PATIENT INFORMATION
YCANTH (WYE' KANTH)
(cantharidin)
topical solution

What is YCANTH?
YCANTH is a prescription medicine used on the skin (topical) to treat molluscum contagiosum (molluscum bumps) in adults and children 2 years of age and older.
It is not known if YCANTH is safe and effective in children under 2 years of age.

Do not receive treatment with YCANTH if you are allergic to any of the ingredients in YCANTH. See the end of this leaflet for a complete list of ingredients in YCANTH.

Before receiving treatment with YCANTH, tell your healthcare provider about all of your medical conditions, including if you:

- are being treated or have had treatments for molluscum bumps.
- have other skin problems.
- are pregnant or plan to become pregnant. It is not known if YCANTH can harm your unborn baby.
- are breastfeeding or plan to breastfeed. Your healthcare provider should avoid applying YCANTH to areas of your skin where your baby could come into contact with YCANTH and get it in their mouth or eyes. Talk to your healthcare provider about whether you should breastfeed while YCANTH is on your skin.

Tell your healthcare provider about all the medications you take, including prescription and over-the-counter medicines, vitamins and herbal supplements.

How will I receive treatment with YCANTH?

- Your healthcare provider will apply YCANTH to the areas on your skin with molluscum bumps.
- YCANTH is for use on the skin (topical use) only. YCANTH is not for use in your mouth, nose, genital areas, or in your eyes.
- You may need more than 1 treatment with YCANTH. Your healthcare provider may apply YCANTH about every 3 weeks as needed.

Preparing for your treatment with YCANTH.

- On the day of treatment, do not apply topical steroids, creams, lotions, or sunscreen to areas with molluscum bumps.

After your healthcare provider applies YCANTH to your molluscum bumps:

- Allow YCANTH to dry completely before leaving your healthcare provider's office or clinic (up to 5 minutes).
- Do not touch the treated areas for 24 hours or until washing.
- Do not allow treated areas of your skin to come into contact with your mouth, nose, genital areas, or your eyes for 24 hours or until washing.
- Do not allow children to lick or bite the treated areas. YCANTH contains a bittering agent to discourage young children from putting it in their mouths. See "What are the ingredients in YCANTH?"
- Do not apply topical steroids, creams, lotions, or sunscreen to treated areas for 24 hours after treatment or until you wash YCANTH off of your skin.
- Do not cover any of the treated areas with bandages.
- YCANTH contains a violet-colored dye. You may temporarily see the violet color on the treated areas of your skin.
- You may take over-the-counter pain relief medicines as needed.
- Wash the treated skin area with soap and water 24 hours after treatment unless your healthcare provider instructs you otherwise. You may wash YCANTH off of your skin sooner if you develop severe blistering, severe pain or other severe reactions. Do not use a washcloth, abrasive material or vigorous rubbing because this could be painful.
- Contact your healthcare provider with any questions.

What should I avoid after receiving treatment with YCANTH?

- Avoid contact with the treated areas of your skin, including contact with your mouth (oral contact).
- Avoid applying other products to the treated areas of your skin until 24 hours after receiving treatment with YCANTH or until after washing YCANTH off of the treated areas of your skin.
- YCANTH is flammable, even after drying. Avoid fire, flame or smoking near lesion(s) during treatment and after treatment until YCANTH is washed off of your skin.

What are the possible side effects of YCANTH?
YCANTH can cause serious side effects, including:

- Serious side effects if YCANTH is swallowed or it comes into contact with your mouth or eyes.

- YCANTH can cause life threatening reactions or death if it gets into your or your child's mouth or is swallowed. These reactions can include:

- kidney failure
- blisters and severe damage to your stomach and intestine (intestinal tract)

- blood clotting problems
- seizures
- a certain type of paralysis

If you or your child swallow (ingest) YCANTH, contact a Poison Control Center (1-800-222-1222) or go to the nearest hospital emergency room right away.

- Eye contact reactions. Severe eye injury can happen if YCANTH gets into your eyes. Contact with YCANTH in the eyes may cause:

- ulcers or small holes in your eyes
- scarring
- redness

- irritation
- severe eye pain
- permanent eye injury, including blindness

If YCANTH accidentally gets into your eyes, flush them well with water for at least 15 minutes and get medical help right away.

- Skin reactions. Skin reactions are common at the areas where you have been treated with YCANTH, but can also sometimes be severe. Skin reactions with YCANTH may include:

- small fluid-filled or non-fluid filled raised blisters on or around treated area(s)
- pain
- itching
- scabs

- redness
- lightening or darkening of the skin in the treated area(s)
- dry skin at the treated area(s)
- swelling on or near the treated area(s)
- breakdown of the outer layer of skin at the treated area(s)

If you develop severe blistering, severe pain or other severe reactions at the treated areas of your or your child's skin, wash YCANTH off of your skin sooner than 24 hours and call your healthcare provider. See "How will I receive treatment with YCANTH?"

Call your doctor for medical advice about side effects. You may report side effects to FDA at 1-800-FDA-1088.
You may also report side effects to Verrica Pharmaceuticals Inc. at 1-877-837-7422.

General information about the safe and effective use of YCANTH.
Medicines are sometimes prescribed for purposes other than those listed in a Patient Information leaflet. You can ask your pharmacist or healthcare provider for information that is written for health professionals.

What are the ingredients in YCANTH?
Active ingredient: cantharidin
Inactive ingredients: acetone, camphor, castor oil, denatonium benzoate, ethanol, gentian violet, hydroxypropyl cellulose, and nitrocellulose. The inactive ingredient denatonium benzoate is a bittering agent to discourage young children from putting it in their mouths and accidentally swallowing YCANTH.
Manufactured by: Pharmaceutical Packaging Solutions, 341 JD Yarnell Industrial Pkwy, Clinton, TN 37716
For: Verrica Pharmaceuticals Inc., 44 West Gay Street, Suite 400, West Chester, PA 19380.
YCANTH and VERRICA are registered trademarks of Verrica Pharmaceuticals Inc.
Copyright © 2024 Verrica Pharmaceuticals Inc.
All rights reserved

This Patient Information has been approved by the U.S. Food and Drug Administration.

Issued: 10/2024

PRINCIPAL DISPLAY PANEL - 12 Ampule Applicator Package Carton

FOR ADMINISTRATION BY A HEALTHCARE PROFESSIONAL ONLY

NDC 71349-070-12
Rx Only

12 Applicators
and 2 Break Tools

Ycanth®
(cantharidin)
TOPICAL
SOLUTION 0.7%

Single use applicator contains
approximately 0.45 mL of 0.7% cantharidin solution.
Each 1 mL of solution contains 7 mg cantharidin.
Recommended Dosage: See prescribing information.
For Topical Use Only.

- WARNING: Flammable liquid, even after drying. Avoid
  fire, flame or smoking near lesion(s) during treatment
  and after application until removed.
- WARNING: Highly Toxic! For Topical Use Only.
  YCANTH can be fatal if administered orally or taken
  internally.
- Wear gloves and eye protection during YCANTH®
  preparation and administration.
- Remove the paperboard sleeve and inspect the
  applicator before using the break tool.
- If YCANTH contacts healthy skin, immediately
  remove by wiping with a cotton swab or gauze.
- If YCANTH gets in the eyes, flush eyes with water
  for at least 15 minutes and seek medical attention.

PRINCIPAL DISPLAY PANEL - 6 Ampule Applicator Package Carton

FOR ADMINISTRATION BY A HEALTHCARE PROFESSIONAL ONLY

NDC 71349-999-06
Rx Only

6 Applicators
and 2 Break Tools

Ycanth®
(cantharidin)
TOPICAL
SOLUTION 0.7%

Single use applicator contains
approximately 0.45 mL of 0.7% cantharidin solution.
Each 1 mL of solution contains 7 mg cantharidin.
Recommended Dosage: See prescribing information.
For Topical Use Only.

Professional Sample. Not for Sale.

- WARNING: Flammable liquid, even after drying. Avoid
  fire, flame or smoking near lesion(s) during treatment
  and after application until removed.
- WARNING: Highly Toxic! For Topical Use Only.
  YCANTH can be fatal if administered orally or taken
  internally.
- Wear gloves and eye protection during YCANTH®
  preparation and administration.
- Remove the paperboard sleeve and inspect the
  applicator before using the break tool.
- If YCANTH contacts healthy skin, immediately
  remove by wiping with a cotton swab or gauze.
- If YCANTH gets in the eyes, flush eyes with water
  for at least 15 minutes and seek medical attention.